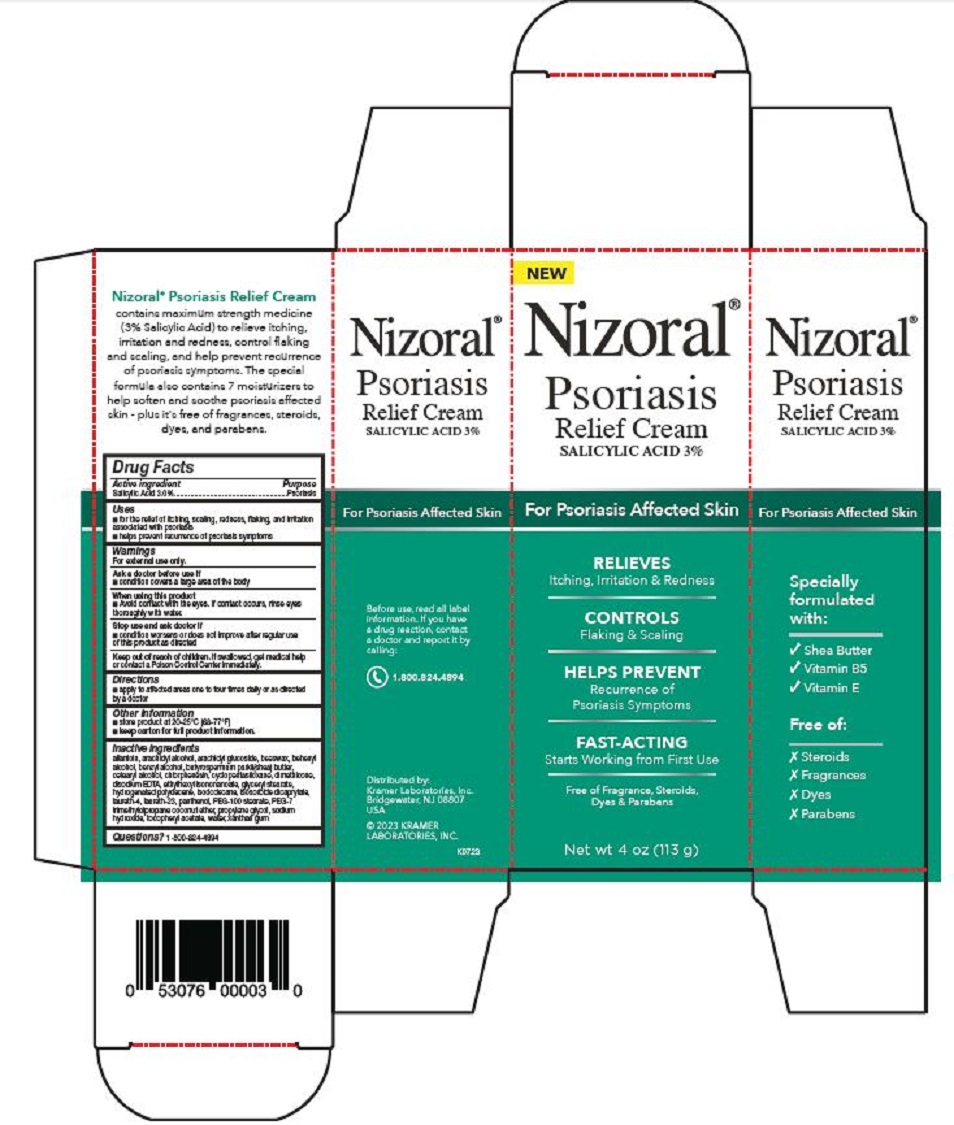 DRUG LABEL: Nizoral Psoriasis Relief
NDC: 55505-224 | Form: CREAM
Manufacturer: Kramer Laboratories
Category: otc | Type: HUMAN OTC DRUG LABEL
Date: 20251223

ACTIVE INGREDIENTS: Salicylic Acid 3 g/100 g
INACTIVE INGREDIENTS: Allantoin; Arachidyl Alcohol; Arachidyl Glucoside; Yellow Wax; Benzyl Alcohol; Shea Butter; Cetostearyl Alcohol; Chlorphenesin; Cyclomethicone 5; Dimethicone; Disodium Edta-Copper; Edetate Disodium Anhydrous; Glyceryl Stearate Citrate; Hydrogenated Polydecene Type I; Isododecane; Isosorbide Dicaprylate; Laureth-4; Laureth-23; Panthenol; Peg-100 Stearate; Peg-7 Trimethylolpropane Coconut Ether; Propylene Glycol; Sodium Hydroxide; .Alpha.-Tocopherol Acetate; Water; Xanthan Gum

Drug Facts

ACTIVE INGREDIENT

Active ingredient | Purpose
Salicylic Acid 3.0% | Psoriasis

Uses

- for the relief of itching, scaling, redness, flaking, and irritation associated with psoriasis
- helps prevent recurrence of psoriasis symptoms

Warnings
For external use only

Ask a doctor before use if

- condition covers a large area of the body

When using this product

- Avoid contact with the eyes. If contact occurs, rinse eyes thoroughly with water.

Stop use and ask doctor if

- condition worsens or does not improve after regular use of this product as directed

KEEP OUT OF REACH OF CHILDREN

Keep out of the reach of children. If swallowed, get medical help or contact a Poison Control Center immediately.

Directions

- apply to affected areas one to four times daily or as directed by a doctor

Other information

- store product at 20-25°C (68-77°F)
- keep carton for full product information.

Inactive ingredients

allantoin, arachidyl alcohol, arachidyl glucoside, beeswax, behenyl alcohol, benzyl alcohol, butyrospermum parkii(shea) butter, cetearyl alcohol, chlorphenesin, cyclopentasiloxane, dimethicone, disodium EDTA, ethylhexyl isononanoate, glyceryl stearate, hydrogenated polydecene, isododecane, isosorbide dicaprylate, laureth-4, laureth-23, panthenol, PEG-100 stearate, PEG-7 trimethylolpropane coconut ether, propylene glycol, sodium hydroxide, tocopheryl acetate, water, xanthan gum

Questions? 1-800-824-4894

PRINCIPAL DISPLAY PANEL

NEW
Nizoral®
Psoriasis
Relief Cream
SALICYLIC ACID 3%
For Psoriasis Affected Skin
RELIEVES
Itching, Irritation & Redness
CONTROLS
Flaking & Scaling
HELPS PREVENT
Recurrence of
Psoriasis Symptoms
FAST-ACTING
Starts Working from First Use
Free of Fragrance, Steroids,
Dyes & Parabens
Net wt 4 oz (113 g)
Specially
formulated
with:
√ Shea Butter
√ Vitamin B5
√ Vitamin E
Free of:
Ⅹ Steroids
Ⅹ Fragrances
Ⅹ Dyes
Ⅹ Parabens
Before use, read all label
information. If you have
a drug reaction, contact
a doctor and report it by
calling:
1.800.824.4894
Distributed by:
Kramer Laboratories, Inc.
Bridgewater, NJ 08807
USA
© 2023 KRAMER
LABORATORIES, INC.
K0723